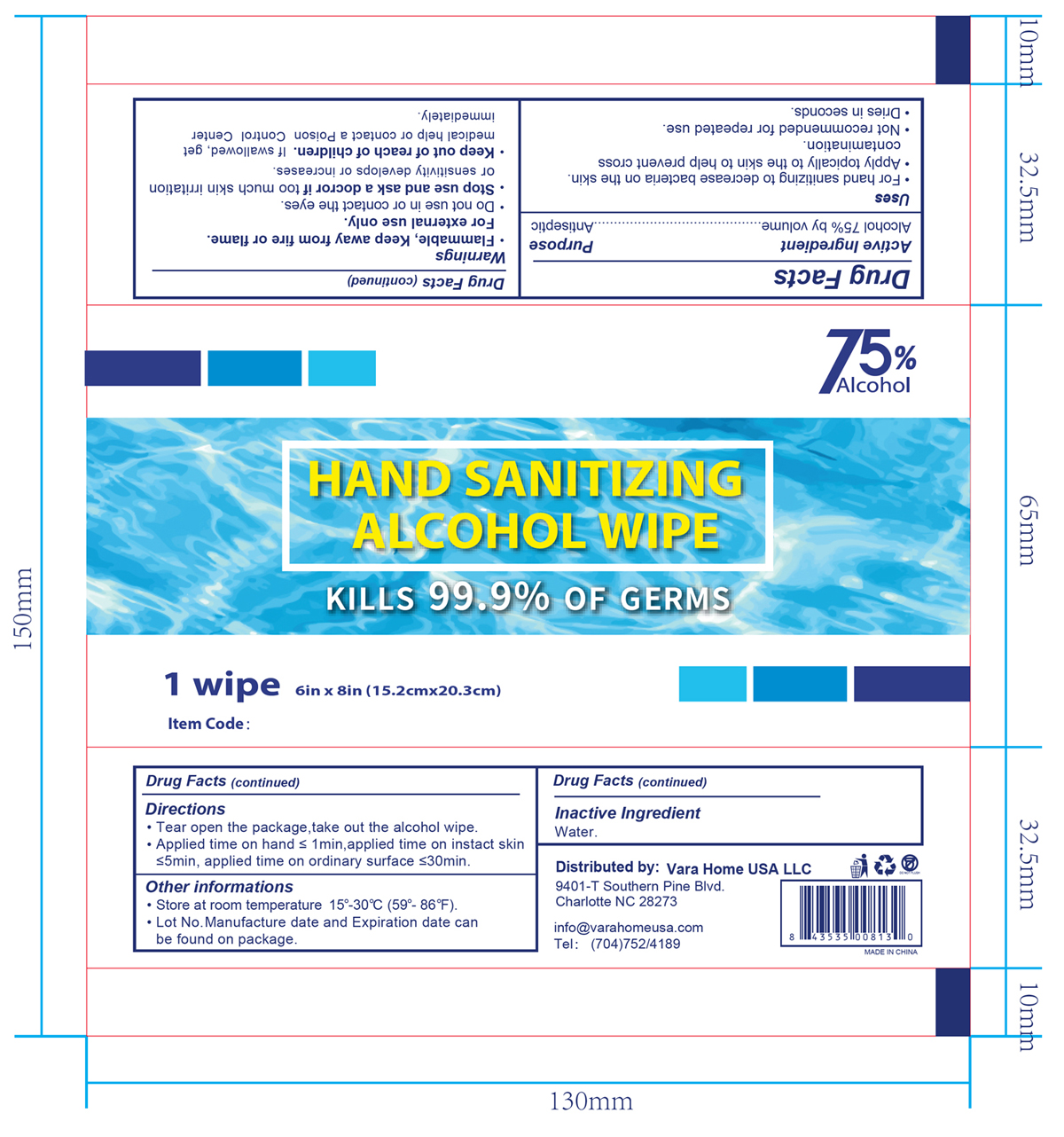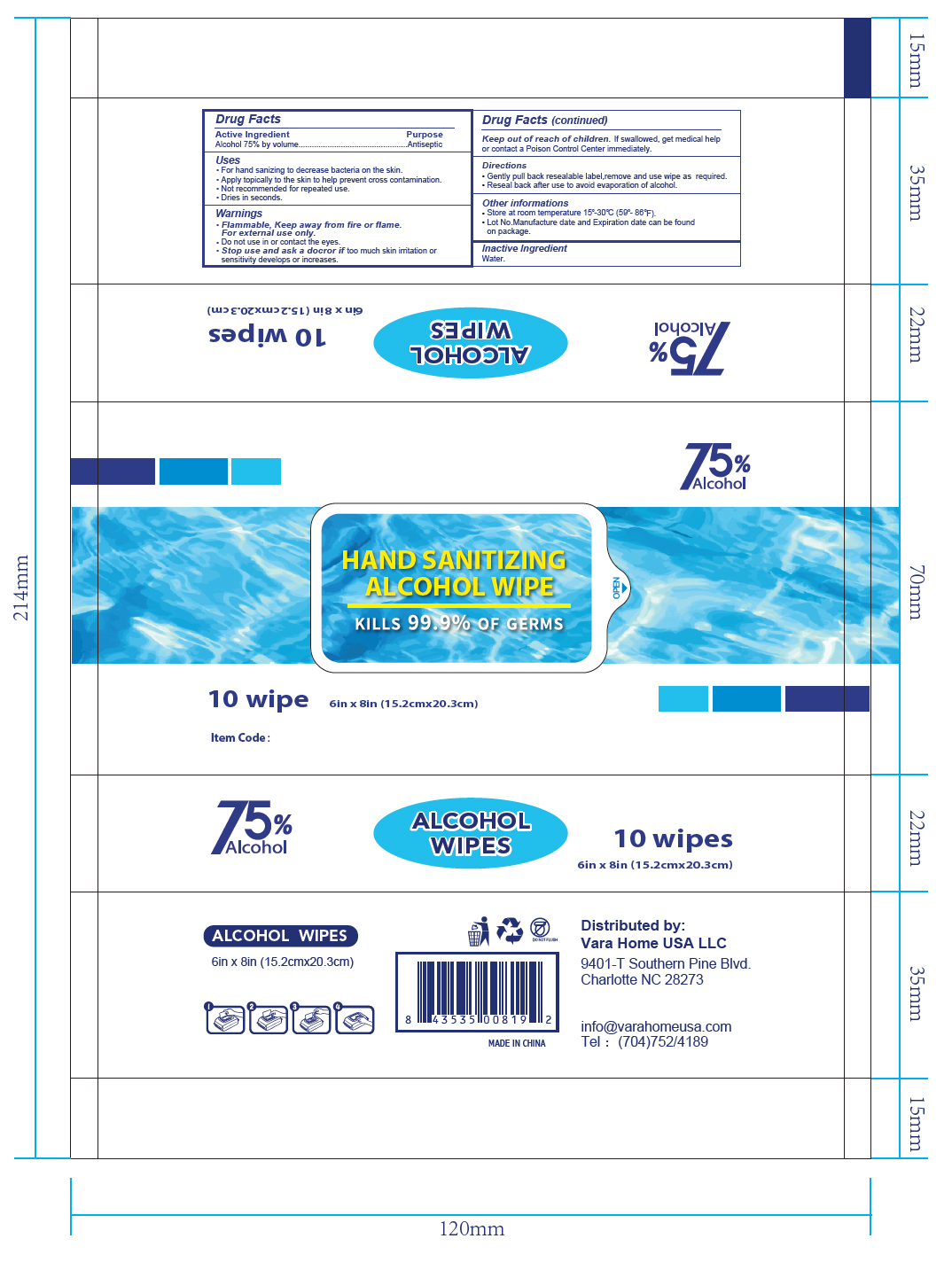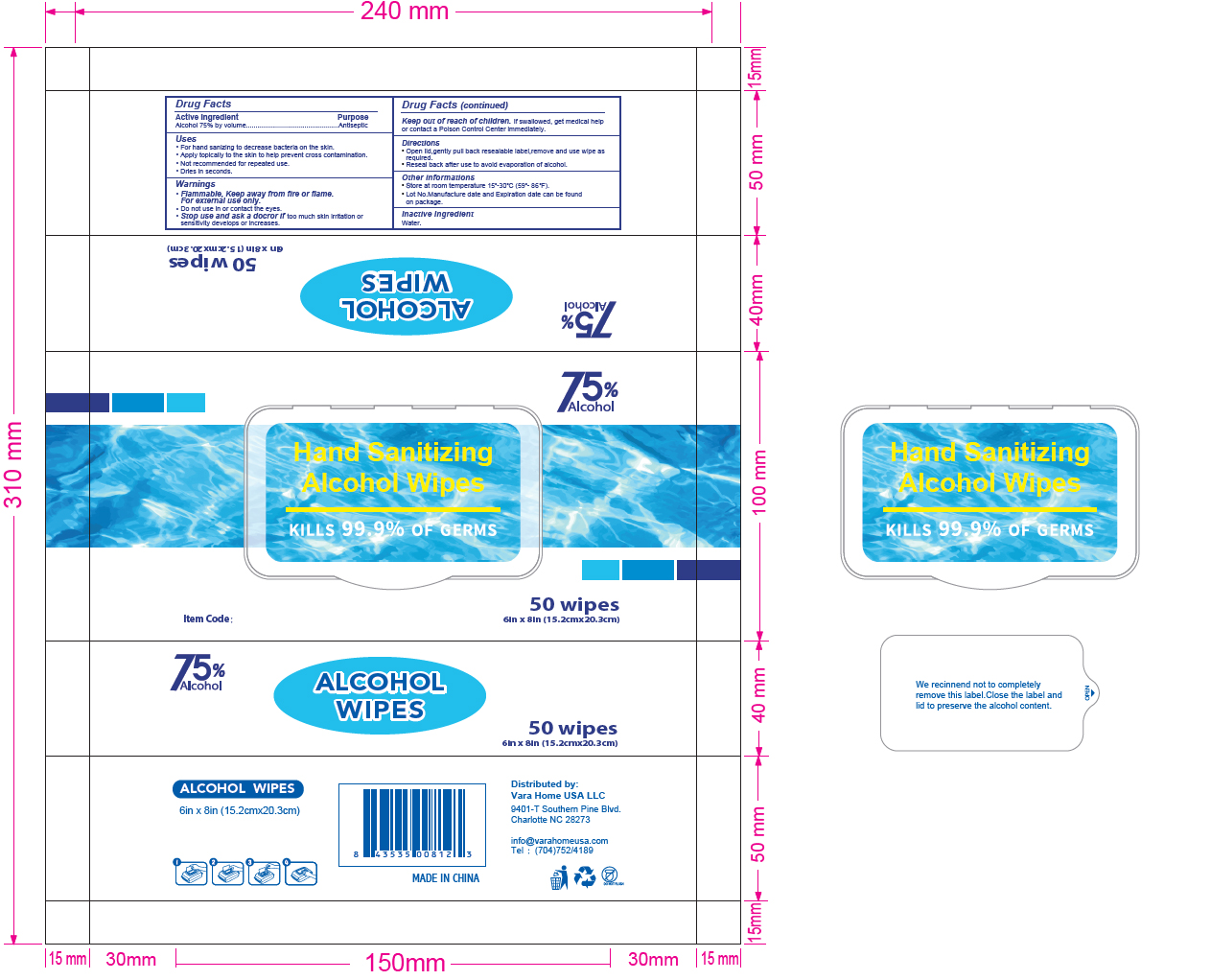 DRUG LABEL: Alcohol Wipes
NDC: 79060-001 | Form: CLOTH
Manufacturer: Vara Home Usa Llc
Category: otc | Type: HUMAN OTC DRUG LABEL
Date: 20200612

ACTIVE INGREDIENTS: ALCOHOL 0.75 mL/1 g
INACTIVE INGREDIENTS: WATER

Alcohol Wipes

Active Ingredient(s)

Alcohol 75% v/v. Purpose: Antiseptic

Purpose

Antiseptic, Alcohol wipes

Use

• For hand santitizing to decrease bacteria on the skin.
• Apply topically to the skin to help prevent cross contamination.
• Not recommended for repeated use.
• Dries in seconds.

Warnings

Flammable. Keep away from fire or flame.

For external use only.

Do not use

in or contact the eyes.

Stop use and ask a doctor

if too much skin irritation and sensitivity develops or increases

Keep out of reach of children. If swallowed, get medical help or contact a Poison Control Center right away.

Directions

- Gently pull back resealable label, remove and use wipe as required.
- Reseal back after use to avoid evaporation of alcohol.

Other information

- Store at room temperature 15-30℃ (59-86°F).
- Lot No. Manufacture date and expiration date can be found on package.

Inactive ingredients

water

Package Label - Principal Display Panel

1 wipe NDC: 79060-001-01

10 wipes NDC: 79060-001-02

50 wipes NDC: 79060-001-03